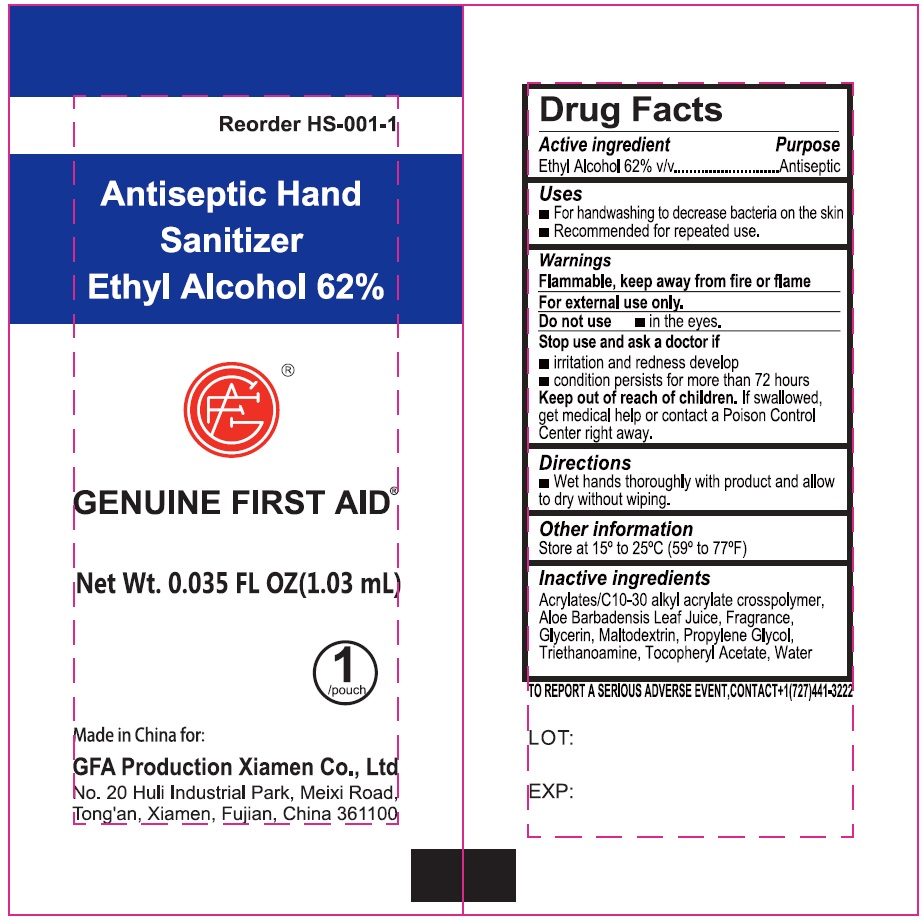 DRUG LABEL: Genuine First Aid Hand Sanitizer
NDC: 50814-078 | Form: CREAM
Manufacturer: GFA Production(Xiamen) Co.,Ltd
Category: otc | Type: HUMAN OTC DRUG LABEL
Date: 20251107

ACTIVE INGREDIENTS: ALCOHOL 62 mL/100 mL
INACTIVE INGREDIENTS: ALOE VERA LEAF; GLYCERIN; MALTODEXTRIN; PROPYLENE GLYCOL; TROLAMINE; .ALPHA.-TOCOPHEROL ACETATE; WATER

Genuine First Aid Hand Sanitizer

Active ingredient

Ethyl Alcohol 62% v/v

Purpose

Antiseptic

Uses

- For handwashing to decrease bacteria on the skin
- Recommended for repeated use.

Warnings

Flammable, keep away from fire or flame

For external use only.

Do not use

- in the eyes.

Stop use and ask a doctor if

- irritation and redness develop
- condition persists for more than 72 hours

Keep out of reach of children.

If swallowed, get medical help or contact a Poison Control Center right away.

Directions

- Wet hands thoroughly with product and allow to dry without wiping.

Other information

Store at 15° to 25°C (59° to 77°F)

Inactive ingredients

Acrylates/C 10-30 alkyl acrylate crosspolymer, Aloe Barbadensis Leaf Juice, Fragrance, Glycerin, Maltodextrin, Propylene Glycol, Triethanoamine, Tocopheryl Acetate, Water